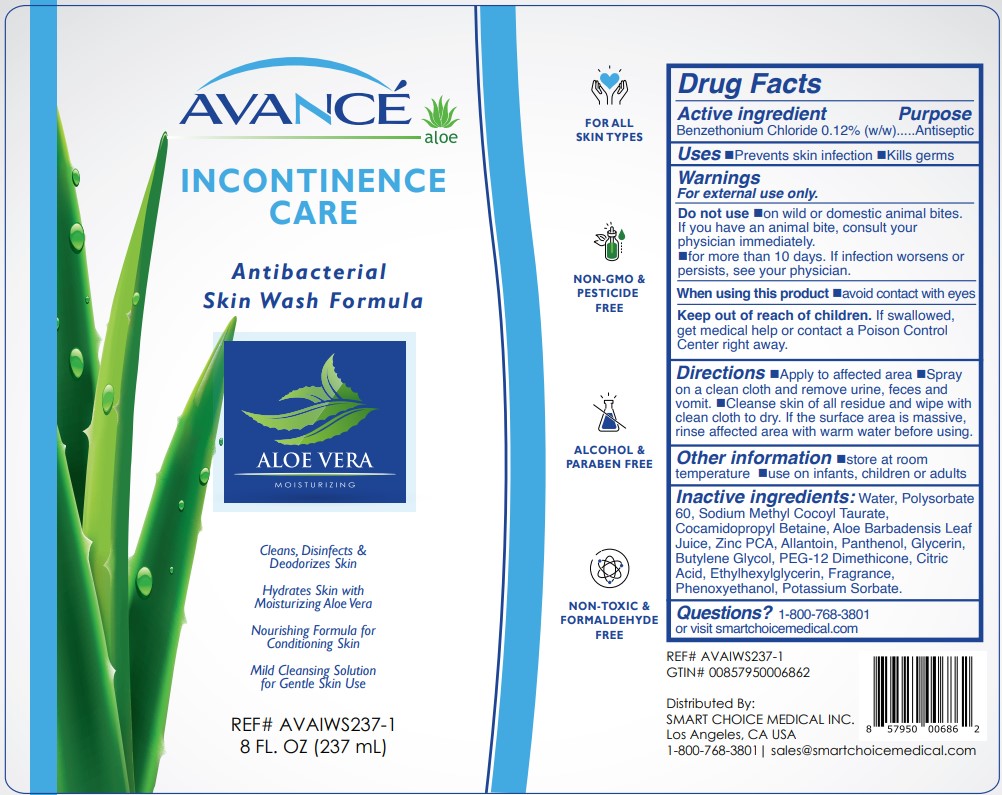 DRUG LABEL: AVANCE INCONTINENCE CARE
NDC: 70936-112 | Form: SOLUTION
Manufacturer: SMART CHOICE MEDICAL INC.
Category: otc | Type: HUMAN OTC DRUG LABEL
Date: 20260112

ACTIVE INGREDIENTS: BENZETHONIUM CHLORIDE 0.12 g/100 g
INACTIVE INGREDIENTS: POLYSORBATE 60; ZINC PIDOLATE; ALLANTOIN; POTASSIUM SORBATE; PEG-12 DIMETHICONE; ANHYDROUS CITRIC ACID; SODIUM METHYL COCOYL TAURATE; COCAMIDOPROPYL BETAINE; PANTHENOL; PHENOXYETHANOL; ETHYLHEXYLGLYCERIN; WATER; ALOE VERA LEAF; GLYCERIN; BUTYLENE GLYCOL

SMART CHOICE MEDICAL - AVANCE INCONTINENCE CARE SPRAY (70936-112)

ACTIVE INGREDIENT

BENZETHONIUM CHLORIDE 0.12% (W/W)

PURPOSE

ANTISEPTIC

USES

- PREVENTS SKIN INFECTION
- KILLS GERMS

WARNINGS

- FOR EXTERNAL ONLY

DO NOT USE:

- ON WILD OR DOMESTIC ANIMAL BITES. IF YOU HAVE AN ANIMAL BITE, CONSULT YOUR PHYSICIAN IMMEDIATELY.
- ON INFECTIONS
- FOR MORE THAN 10 DAYS. IF INFECTION WORSENS OR PERSISTS, SEE YOUR PHYSICIAN.

WHEN USING THIS PRODUCT:

- AVOID CONTACT WITH EYES

KEEP OUT OF REACH OF CHILDREN

KEEP OUT OF REACH OF CHILDERN. IF SWALLOWED GET MEDICAL HELP OR CONTACT A POISON CONTROL CENTER RIGHT AWAY

DIRECTIONS

- Apply to affected area
- Spray on a clean cloth and remove urine, feces and vomit.
- Cleanse skin of all residue and wipe with clean cloth to dry. If the surface area is massive, rinse affected area with warm water before using.

OTHER INFORMATION

- STORE AT ROOM TEMPERATURE
- USE ON INFANTS, CHILDREN OR ADULTS

INACTIVE INGREDIENTS

Water, Polysorbate 60, Sodium Methyl Cocoyl Taurate, Cocamidopropyl Betaine, Aloe Barbadensis Leaf Juice, Zinc PCA, Allantoin, Panthenol, Glycerin, Butylene Glycol, PEG-12 Dimethicone, Citric Acid, Ethylhexylglycerin, Fragrance, Phenoxyethanol, Potassium Sorbate.

QUESTIONS?

1-800-768-3801
or visit smartchoicemedical.com